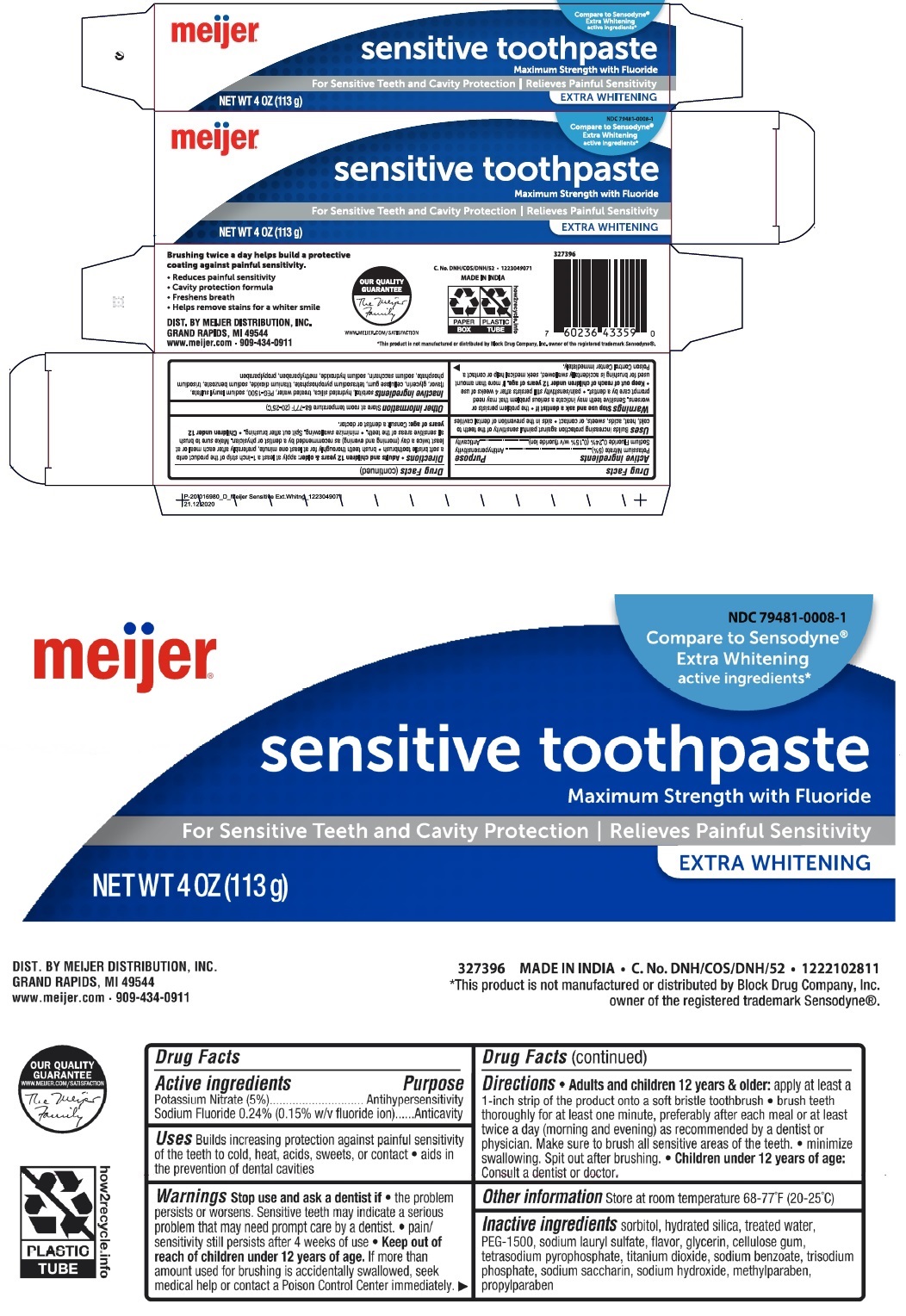 DRUG LABEL: Sensitive Whitening Tooth-paste
NDC: 79481-0008 | Form: PASTE, DENTIFRICE
Manufacturer: Meijer, Inc.
Category: otc | Type: HUMAN OTC DRUG LABEL
Date: 20251223

ACTIVE INGREDIENTS: POTASSIUM NITRATE 50 mg/1 g; SODIUM FLUORIDE 2.43 mg/1 g
INACTIVE INGREDIENTS: SORBITOL; HYDRATED SILICA; WATER; POLYETHYLENE GLYCOL 1600; SODIUM LAURYL SULFATE; GLYCERIN; CARBOXYMETHYLCELLULOSE SODIUM, UNSPECIFIED; SODIUM PYROPHOSPHATE; TITANIUM DIOXIDE; SODIUM BENZOATE; SODIUM PHOSPHATE, TRIBASIC, ANHYDROUS; SACCHARIN SODIUM; SODIUM HYDROXIDE; METHYLPARABEN; PROPYLPARABEN

meijer® sensitive toothpaste EXTRA WHITENING

Active ingredients

Potassium Nitrate (5%)

Sodium Fluoride 0.24% (0.15% w/v fluoride ion)

Purpose

Antihypersensitivity

Anticavity

Uses

Builds increasing protection against painful sensitivity of the teeth to cold, heat, acids, sweets, or contact • aids in the prevention of dental cavities

Warnings

Stop use and ask a dentist if • the problem persists or worsens. Sensitive teeth may indicate a serious problem that may need prompt care by a dentist • pain/sensitivity still persists after 4 weeks of use

• Keep out of reach children under 12 years of age.

If more than amount used for brushing is accidentally swallowed, seek medical help or contact a Poison Control Center immediately.

Directions

• Adults and children 12 years & older: apply at least a 1-inch strip of the product onto a soft bristle toothbrush • brush teeth thoroughly for at least one minute, preferably after each meal or at least twice a day (morning and evening) as recommended by a dentist or physician. Make sure to brush all sensitive areas of the teeth. • minimize swallowing. Spit out after brushing. • Children under 12 years of age: Consult a dentist or doctor.

Other information

Store at room temperature 68-77°F (20-25°C)

Inactive ingredients

sorbitol, hydrated silica, treated water, PEG-1500, sodium lauryl sulfate, flavor, glycerin, cellulose gum, tetrasodium pyrophosphate, titanium dioxide, sodium benzoate, trisodium phosphate, sodium saccharin, sodium hydroxide, methylparaben, propylparaben

Compare to Sensodyne®

Extra Whitening active ingredients*

Maximum Strength with Fluoride

For Sensitive Teeth and Cavity Protection | Relieves Painful Sensitivity

Brushing twice a day helps build a protective coating against painful sensitivity.

• Reduces painful sensitivity

• cavity protection formula

• Freshens breath

• Helps remove stains for a whiter smile

DIST. BY MEIJER DISTRIBUTION, INC.

GRAND RAPIDS, MI 49544

www.meijer.com • 909-434-0911

OUR QUALITY GUARANTEE

WWW.MEIJER.COM/SATISFACTION

MADE IN INDIA

PAPER BOX

PLASTIC TUBE

how2recycle.info

*This product is not manufactured or distributed by Block Drug Company, Inc. owner of the registered trademark Sensodyne®.